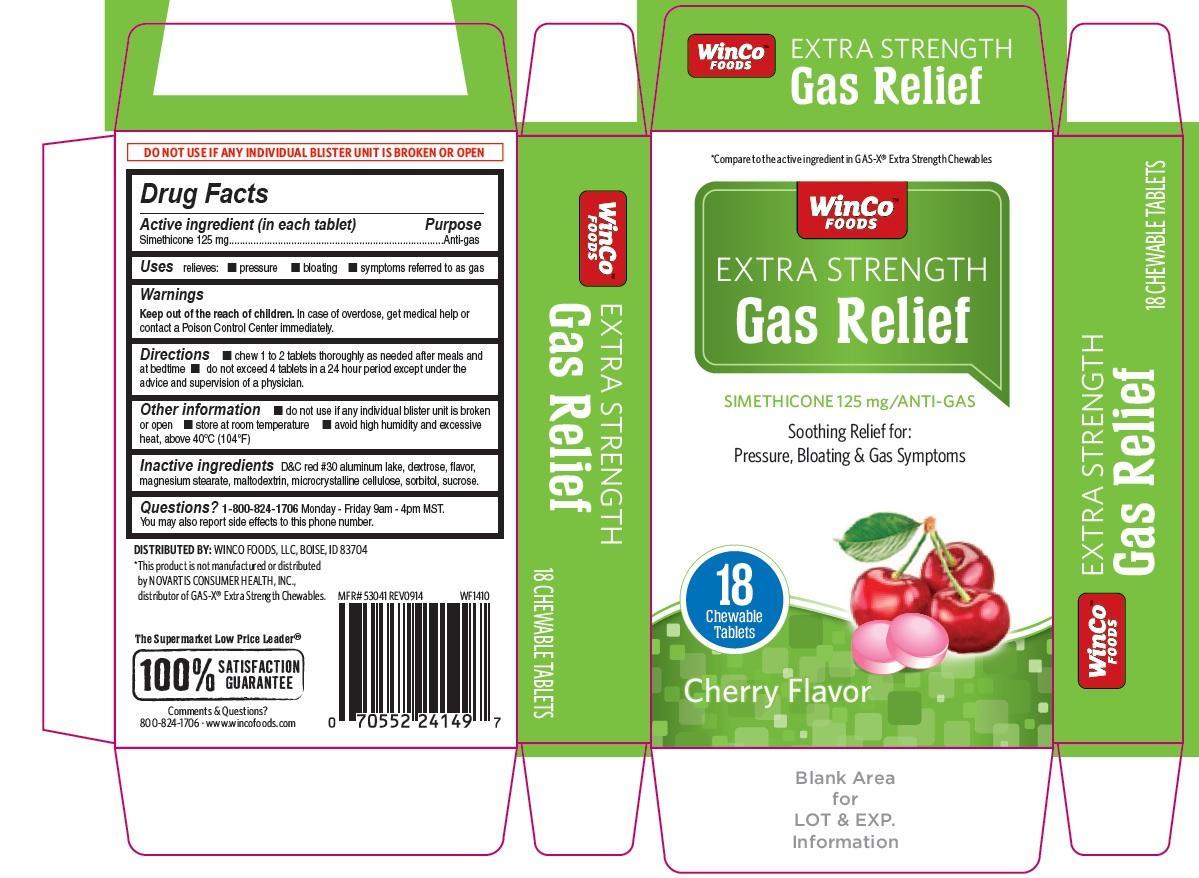 DRUG LABEL: Gas Relief Extra Strength Cherry
NDC: 67091-232 | Form: TABLET, CHEWABLE
Manufacturer: WinCo Foods, LLC
Category: otc | Type: HUMAN OTC DRUG LABEL
Date: 20220114

ACTIVE INGREDIENTS: DIMETHICONE 125 mg/1 1
INACTIVE INGREDIENTS: D&C RED NO. 30; DEXTROSE, UNSPECIFIED FORM; MAGNESIUM STEARATE; MALTODEXTRIN; MICROCRYSTALLINE CELLULOSE; SORBITOL; SUCROSE

Extra strength Gas Relief Cherry Tablets

Active ingredient (in each tablet)

Simethicone 125 mg

Purpose

Anti-gas

Uses

relieves:

- pressure
- bloating
- symptoms referred to as gas

Warnings

Keep out of the reach of children. In case of overdose, get medical help or contact a poison control center immediately.

Directions

- chew 1 to 2 tablets thoroughly as needed after meals and at bedtime
- do not exceed 4 tablets in a 24 hour period except under the advice and supervision of a physician

Other information

- do not use if any individual blister unit is broken or open
- store at room temperature
- avoid high humidity and excessive heat, above 40oC (104oF)

Inactive ingredients

D&C red 30 aluminum lake, dextrose, flavor, magnesium stearate, maltodextrin, microcrystalline cellulose, sorbitol, sucrose

Questions?

1-800-824-1706 Monday -Friday 9am - 4pm MST.

You may also report side effects to this phone number

Principal Display Panel

*Compare to the active ingredient in GAS-X®Extra strength Chewables

EXTRA STRENGTH

Gas Relief

SIMETHICONE 125 mg /ANTI-GAS

Soothing Relief for: Pressure, Bloating & Gas Symptoms

Cherry Flavor

18 chewable tablets